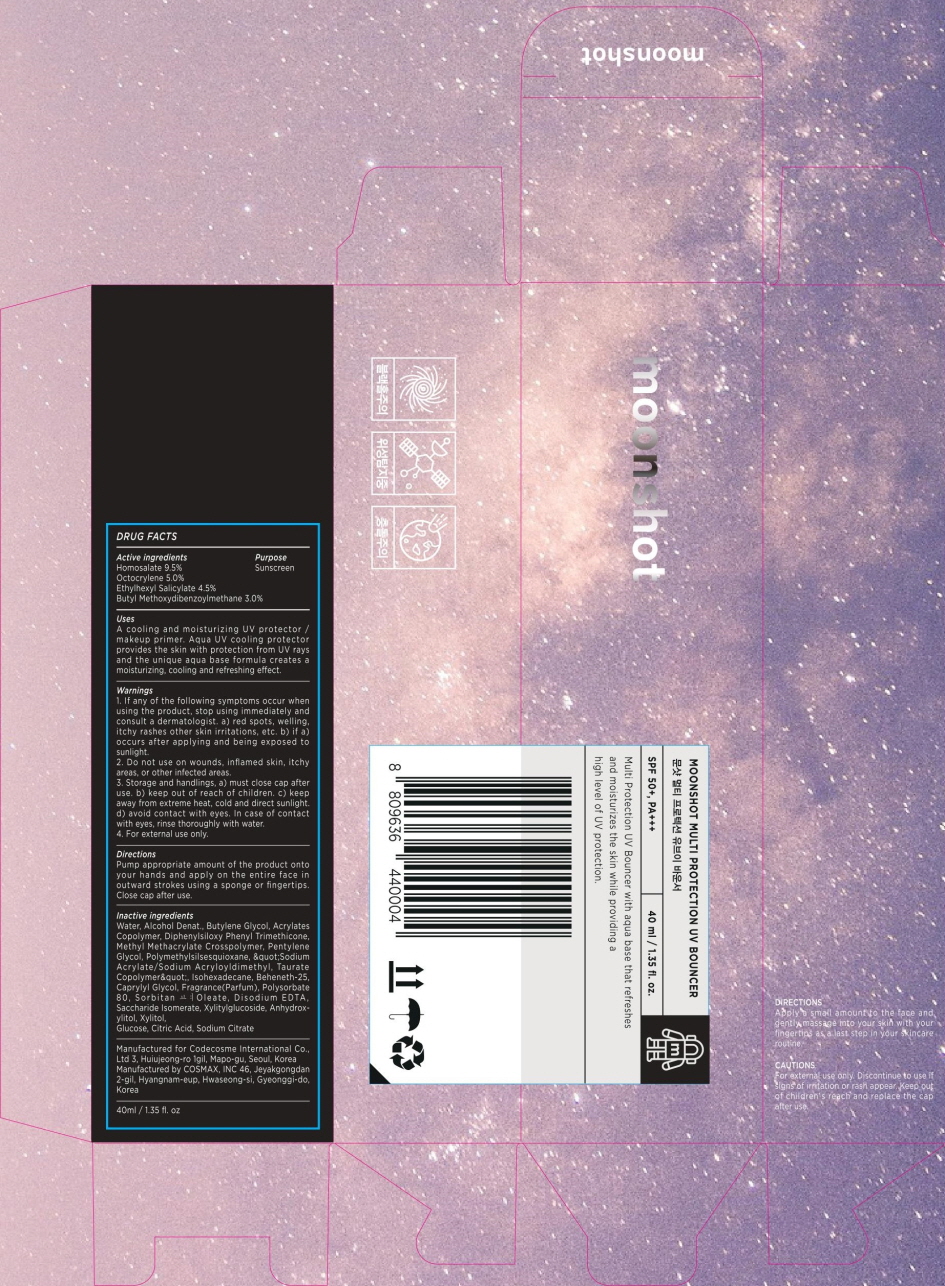 DRUG LABEL: Moonshot Multi Protection UV Bouncer
NDC: 71786-060 | Form: CREAM
Manufacturer: Codecosme International Co., Ltd.
Category: otc | Type: HUMAN OTC DRUG LABEL
Date: 20190121

ACTIVE INGREDIENTS: Homosalate 3.80 g/40 mL; Octocrylene 2.00 g/40 mL; Octisalate 1.80 g/40 mL; Avobenzone 1.20 g/40 mL
INACTIVE INGREDIENTS: Water; Butylene Glycol

ACTIVE INGREDIENT

Active ingredients: Homosalate 9.5%, Octocrylene 5.0%, Ethylhexyl Salicylate 4.5%, Butyl Methoxydibenzoylmethane 3.0%

INACTIVE INGREDIENT

Water, Alcohol Denat., Butylene Glycol, Acrylates Copolymer, Diphenylsiloxy Phenyl Trimethicone, Methyl Methacrylate Crosspolymer, Pentylene Glycol, Polymethylsilsesquioxane, "Sodium Acrylate/Sodium Acryloyldimethyl, Taurate Copolymer", Isohexadecane, Beheneth-25, Caprylyl Glycol, Fragrance(Parfum), Polysorbate 80, Sorbitan Oleate, Disodium EDTA, Saccharide Isomerate, Xylitylglucoside, Anhydroxylitol, Xylitol, Glucose, Citric Acid, Sodium Citrate

PURPOSE

Purpose: Sunscreen

WARNINGS

1. If any of the following symptoms occur when using the product, stop using immediately and consult a dermatologist. a) red spots, swelling, itchy rashes other skin irritations, etc. b) if a) occurs after applying and being exposed to sunlight. 2. Do not use on wounds, inflamed skin, itchy areas, or other infected areas. 3. Storage and handling: a) must close cap after use. b) Keep out of reach of children. c) keep away from extreme heat, cold and direct sunlight. d) Avoid contact with eyes. In case of contact with eyes, rinse thoroughly with water. 4. For external use only.

DESCRIPTION

Uses:

A cooling and moisturizing UV protector / makeup primer.
Aqua UV cooling protector provides the skin with protection from UV rays and the unique aqua base formula creates a moisturizing, cooling and refreshing effect.

Directions:

Pump appropriate amount of the product onto your hands and apply on the entire face in outward strokes using a sponge or fingertips. Close cap after use.